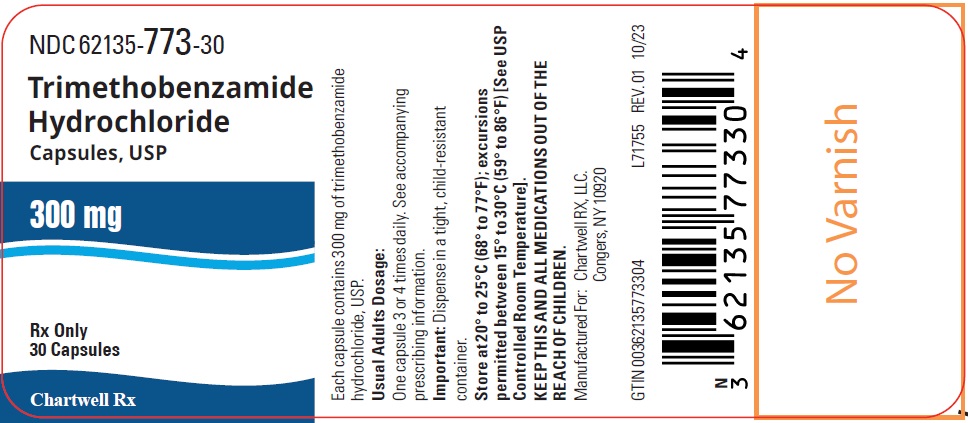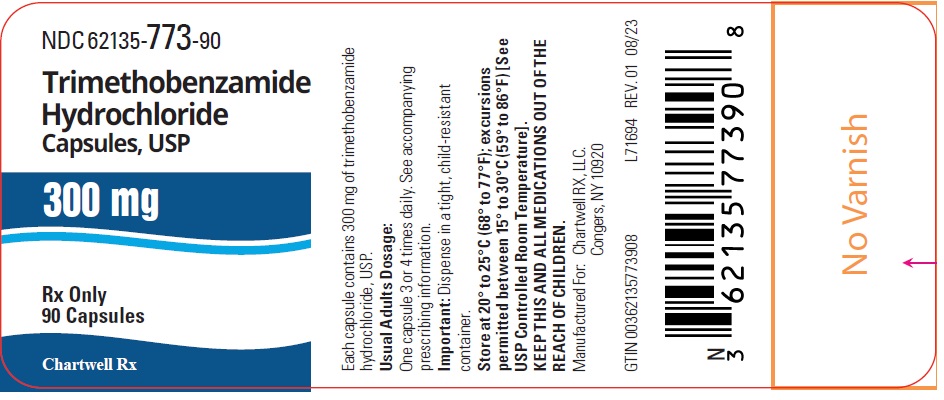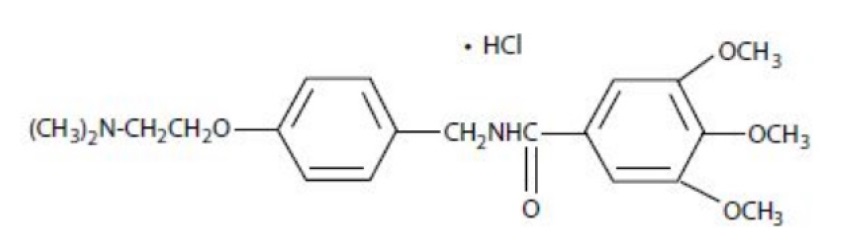 DRUG LABEL: Trimethobenzamide Hydrochloride
NDC: 62135-773 | Form: CAPSULE
Manufacturer: Chartwell RX, LLC
Category: prescription | Type: HUMAN PRESCRIPTION DRUG LABEL
Date: 20251211

ACTIVE INGREDIENTS: TRIMETHOBENZAMIDE HYDROCHLORIDE 300 mg/1 1
INACTIVE INGREDIENTS: ISOPROPYL ALCOHOL; LACTOSE MONOHYDRATE; MAGNESIUM STEARATE; STARCH, CORN; GELATIN, UNSPECIFIED; TITANIUM DIOXIDE; D&C RED NO. 28; FD&C BLUE NO. 1; SODIUM LAURYL SULFATE; SHELLAC; DEHYDRATED ALCOHOL; PROPYLENE GLYCOL; AMMONIA; POTASSIUM HYDROXIDE; BUTYL ALCOHOL

HIGHLIGHTS OF PRESCRIBING INFORMATION

Trimethobenzamide Hydrochloride Capsules, USP
These highlights do not include all the information needed to use TRIMETHOBENZAMIDE HYDROCHLORIDE CAPSULES safely and effectively. See full prescribing information for TRIMETHOBENZAMIDE HYDROCHLORIDE CAPSULES.
TRIMETHOBENZAMIDE hydrochloride capsule, for oral use
Initial U.S. Approval: 1974

1 INDICATIONS AND USAGE

Trimethobenzamide hydrochloride capsules are an antiemetic indicated in adults for the treatment of postoperative nausea and vomiting and for nausea associated with gastroenteritis. (1)

Limitation of Use:

- Trimethobenzamide hydrochloride capsule is not recommended for use in pediatric patients due to the risk of extrapyramidal signs and symptoms and other serious central nervous system (CNS) effects and the risk of exacerbation of the underlying disease in pediatric patients with Reye’s syndrome or other hepatic impairment. (1, 8.4)

2 DOSAGE AND ADMINISTRATION

- The recommended adult dosage is 300 mg orally three or four times daily. (2.1)
- Geriatric patients and/or patients with renal impairment (creatinine clearance 70 mL/min/1.73m^2or less): Reduce the daily dosage by increasing the dosing interval; monitor renal function. (2.2, 8.5, 8.6)
- Select the lowest effective daily dosage and adjust as needed based upon therapeutic response and tolerability. (2.1, 2.2)

3 DOSAGE FORMS AND STRENGTHS

Capsules: 300 mg of trimethobenzamide hydrochloride (3)

4 CONTRAINDICATIONS

Known hypersensitivity to trimethobenzamide (4)

5 WARNINGS AND PRECAUTIONS

- Acute Dystonic Reactions and Other Extrapyramidal Symptoms (EPS):Depending on the severity of symptoms, reduce the dosage or discontinue the drug. Treat acute dystonic reactions with anticholinergics. Avoid trimethobenzamide hydrochloride capsules in patients receiving other drugs that are likely to cause EPS. (5.1, 7.2)
- Masking of Other Serious Disorders:EPS and other CNS symptoms in patients treated with trimethobenzamide hydrochloride capsules may be confused with CNS signs of undiagnosed primary disease (e.g., encephalopathy, metabolic imbalance, Reye’s Syndrome). If CNS symptoms occur, evaluate the risks and benefits of continuing trimethobenzamide hydrochloride capsules. (5.2, 7.2)
- Other CNS Reactions:Coma, depression of mood, disorientation, and seizures have been reported. The recent use of other drugs that cause CNS depression or EPS symptoms may also increase the risk; consider reducing the dosage or discontinuing the drug. (5.3, 7.1, 7.2)
- Hepatotoxicity:Avoid use in patients whose signs and symptoms suggest the presence of hepatic impairment. Discontinue trimethobenzamide hydrochloride capsules in patients who develop impaired liver function while on treatment. (5.4, 8.7)
- Effects on the Ability to Drive or Operate Machinery:Mental and/or physical abilities may be impaired. Concomitant use of other drugs that cause CNS depression or EPS symptoms may increase this effect; either trimethobenzamide hydrochloride capsules or the other interacting drug should be chosen, depending on the importance of the drug to the patient. (5.5, 7.1, 7.2)

6 ADVERSE REACTIONS

Adverse reactions include hypersensitivity reactions and Parkinson-like symptoms; blood dyscrasias, blurring of vision, coma, convulsions, depression of mood, diarrhea, disorientation, dizziness, drowsiness, headache, jaundice, muscle cramps, and opisthotonos. (6)

To report SUSPECTED ADVERSE REACTIONS, contact Chartwell RX, LLC. at 1-845-232-1683 or FDA at 1-800-FDA-1088 or www.fda.gov/medwatch.

7 DRUG INTERACTIONS

- Alcohol:May cause drowsiness; avoid concomitant use. (7.1)
- Other Drugs that Cause CNS Depression or EPS:Either trimethobenzamide hydrochloride capsules or the other interacting drug should be chosen, depending on the importance of the drug to the patient. If CNS-acting drugs cannot be avoided, monitor patients for CNS adverse reactions. (7.2)

FULL PRESCRIBING INFORMATION

1 INDICATIONS AND USAGE

Trimethobenzamide hydrochloride capsules are indicated in adults for the treatment of postoperative nausea and vomiting and for nausea associated with gastroenteritis.

Limitation of Use:

Trimethobenzamide hydrochloride capsules are not recommended for use in pediatric patients due to the risk of extrapyramidal signs and symptoms and other serious central nervous system (CNS) effects, and the risk of exacerbation of the underlying disease in pediatric patients with Reye’s syndrome or other hepatic impairment.

2 DOSAGE AND ADMINISTRATION

2.1 Recommended Adult Dosage

The recommended adult dosage is 300 mg orally three or four times daily. Select the lowest effective daily dosage and adjust as needed based upon therapeutic response and tolerability.

2.2 Dosage Adjustment for Geriatric Patients and/or Patients with Renal Impairment

In geriatric patients and/or in patients with renal impairment (creatinine clearance 70 mL/min/1.73m^2or less), reduce the daily dosage of trimethobenzamide hydrochloride capsules by increasing the dosing interval and adjust as needed based upon therapeutic response and tolerability. Monitor renal function [see Use in Specific Populations (8.5, 8.6)] .

3 DOSAGE FORMS AND STRENGTHS

Capsules: 300 mg trimethobenzamide hydrochloride; size ‘1’, two-piece purple opaque cap and purple opaque body, hard gelatin capsules, printed in white with “HP” on cap and in white with “180” on body, filled with white to off-white granular powder.

4 CONTRAINDICATIONS

Trimethobenzamide hydrochloride capsules are contraindicated in patients with known hypersensitivity to trimethobenzamide [see Adverse Reactions (6)] .

5 WARNINGS AND PRECAUTIONS

5.1 Acute Dystonic Reactions and Other Extrapyramidal Symptoms (EPS)

Extrapyramidal symptoms (EPS), manifested primarily as acute dystonic reactions, may occur with trimethobenzamide hydrochloride capsules. Dystonic reactions may include sudden onset of muscular spasms, especially in the head and neck or opisthotonos. Other EPS include laryngospasm, dysphagia, and oculogyric crisis. Involuntary spasms of the tongue and mouth may lead to difficulty in speaking and swallowing. Anticholinergic drugs can be used to treat acute dystonic reactions.

EPS may also include akathisia, restlessness, akinesia, and other parkinsonian-like symptoms (e.g., tremor). Depending on the severity of symptoms, reduce the daily dosage of trimethobenzamide hydrochloride capsules by increasing the dosing interval or discontinue trimethobenzamide hydrochloride capsules [see Dosage and Administration (2.1)] .

Avoid trimethobenzamide hydrochloride capsules in patients receiving other drugs that are likely to cause EPS (e.g. antipsychotics) [see Drug Interactions (7.2)] .

5.2 Masking of Other Serious Disorders

EPS and other CNS symptoms which can occur in patients treated with trimethobenzamide hydrochloride capsules may be confused with CNS signs of undiagnosed primary disease (e.g., encephalopathy, metabolic imbalance, Reye’s syndrome) [see Warnings and Precautions (5.1, 5.3)] . If CNS symptoms occur, evaluate the risks and benefits of continuing trimethobenzamide hydrochloride capsules for each patient.

5.3 Other CNS Reactions

Other serious CNS adverse reactions such as coma, depression of mood, disorientation, and seizures have been reported with trimethobenzamide hydrochloride capsules administration. The recent use of other drugs that cause CNS depression or EPS symptoms (e.g., alcohol, sedatives, hypnotics, opiates, anxiolytics, antipsychotics, and anticholinergics) may also increase the risk for these serious CNS reactions [see Warnings and Precautions (5.1, 5.5)] . Consider reducing the daily dosage of trimethobenzamide hydrochloride capsules by increasing the dosing interval or discontinuing the drug [see Dosage and Administration (2.1), Drug Interactions (7.1, 7.2)] .

5.4 Hepatotoxicity

Trimethobenzamide hydrochloride is potentially hepatotoxic [see Adverse Reactions (6)] . Avoid use of Trimethobenzamide hydrochloride capsules in patients whose signs and symptoms suggest the presence of hepatic impairment. Discontinue trimethobenzamide hydrochloride capsules in patients who develop impaired liver function while taking trimethobenzamide hydrochloride capsules.

5.5 Effects on the Ability to Drive or Operate Machinery

Trimethobenzamide hydrochloride capsules can cause drowsiness and may impair the mental and/or physical abilities required for the performance of hazardous tasks such as driving a motor vehicle or operating machinery [see Warnings and Precautions (5.1, 5.3)] . Concomitant use of other drugs that cause CNS depression or EPS symptoms (e.g., alcohol, sedatives, hypnotics, opiates, anxiolytics, antipsychotics, and anticholinergics) may increase this effect. Either trimethobenzamide hydrochloride or the other interacting drug should be chosen, depending on the importance of the drug to the patient [Drug Interactions (7.1, 7.2)] . Inform patients not to operate motor vehicles or other dangerous machinery until they are reasonably certain that trimethobenzamide hydrochloride capsules does not affect them adversely.

6 ADVERSE REACTIONS

The following adverse reactions from voluntary reports or clinical studies have been reported with trimethobenzamide. Because many of these reactions were reported voluntarily from a population of uncertain size, it is not always possible to reliably estimate their frequency or establish a causal relationship to drug exposure.

- Nervous system disorders:Parkinson-like symptoms, coma, convulsions, opisthotonos, dizziness, drowsiness, headache, [see Warnings and Precautions (5.1, 5.2, 5.3)]
- Psychiatric disorders:disorientation, depression of mood
- Eye disorders:blurred vision
- Hematologic disorders:blood dyscrasias
- Hepatobiliary disorders:jaundice [see Warnings and Precautions (5.4)]
- Immune system disorders:hypersensitivity, including angioedema and allergic-type skin reactions
- Gastrointestinal disorders:diarrhea
- Musculoskeletal disorders:muscle cramps

7 DRUG INTERACTIONS

7.1 Alcohol

Alcohol may increase the CNS depressant effects of trimethobenzamide hydrochloride capsules and may cause drowsiness [see Warnings and Precautions (5.3, 5.5)] . Avoid concomitant use of trimethobenzamide hydrochloride capsules with alcohol.

7.2 Other Drugs that Cause CNS Depression or EPS

The concurrent use of trimethobenzamide hydrochloride capsules with other drugs that cause CNS depression or EPS (e.g., sedatives, hypnotics, opiates, anxiolytics, antipsychotics, and anticholinergics, may potentiate the effects of trimethobenzamide hydrochloride capsules [see Warnings and Precautions (5.1, 5.2, 5.3, 5.5)] . Either trimethobenzamide hydrochloride capsules or the other interacting drug should be chosen, depending on the importance of the drug to the patient. If CNS-acting drugs cannot be avoided, monitor patients for CNS adverse reactions.

8 USE IN SPECIFIC POPULATIONS

8.1 Pregnancy

Risk Summary

The limited available data with trimethobenzamide in pregnant women are not sufficient to inform a drug-associated risk for major birth defects and miscarriage. No adverse developmental effect was observed in animal reproduction studies with administration of trimethobenzamide hydrochloride during organogenesis in pregnant rats at doses 0.16 and 0.8 times the recommended human dose (RHD) and in pregnant rabbits at doses 1.6 times the RHD [ see Data] .

The estimated background risk of major birth defects and miscarriage for the indicated population is unknown. All pregnancies have a background risk of birth defect, loss, or other adverse outcomes. In the U.S. general population, the estimated background risk of major birth defects and miscarriage in clinically recognized pregnancies is 2 to 4% and 15 to 20%, respectively.

Data

Animal Data

Reproduction studies with trimethobenzamide hydrochloride were conducted in rats and rabbits following administration of trimethobenzamide hydrochloride during organogenesis and no adverse developmental effect was observed in either species. The only effects observed were an increased percentage of embryonic resorptions or stillborn pups in rats administered 20 mg/kg and 100 mg/kg (0.16 and 0.8 times the RHD of 1200 mg/day, based on body surface area) and increased resorptions in rabbits receiving 100 mg/kg (1.6 times the RHD of 1200 mg/day, based on body surface area). In each study, these adverse effects were attributed to one or two dams.

8.2 Lactation

Risk Summary

There is no information on the presence of trimethobenzamide in human milk, the effects of trimethobenzamide hydrochloride capsule on the breastfed infant or the effects of trimethobenzamide hydrochloride capsule on milk production. The lack of clinical data during lactation precludes a clear determination of the risk of trimethobenzamide hydrochloride capsules to an infant during lactation; therefore, the developmental and health benefits of breastfeeding should be considered along with the mother's clinical need for trimethobenzamide hydrochloride capsules and any potential adverse effects on the breastfed infant from trimethobenzamide hydrochloride capsules or from the underlying maternal condition.

8.4 Pediatric Use

The safety and effectiveness of trimethobenzamide hydrochloride capsules in pediatric patients has not been established. Trimethobenzamide hydrochloride capsules are not recommended for use in pediatric patients due to the risk of EPS and other serious CNS effects, and the risk of exacerbation of underlying disease in pediatric patients with Reye’s Syndrome, or other hepatic impairment [see Warnings and Precautions (5.1, 5.2, 5.3, 5.4)] .

8.5 Geriatric Use

Clinical studies of trimethobenzamide did not include sufficient numbers of patients aged 65 years and over to determine whether they respond differently from younger patients. Although there are studies reported in the literature that included geriatric patients 65 years and older with younger patients, it is not known if there are differences in efficacy or safety parameters for geriatric and non-geriatric patients treated with trimethobenzamide hydrochloride capsules. Trimethobenzamide is excreted by the kidney, and the risk of adverse reactions to this drug may be greater in patients with impaired renal function. Because geriatric patients are more likely to have decreased renal function, reduce the daily dosage of trimethobenzamide hydrochloride capsules by increasing the dosing interval and adjust as needed based upon therapeutic response and tolerability. Monitor renal function [see Dosage and Administration (2.2), Use in Specific Populations (8.6)] .

8.6 Renal Impairment

Trimethobenzamide is eliminated by renal excretion [see Clinical Pharmacology (12.3)] . In patients with renal impairment (creatinine clearance 70 mL/min/1.73m^2or less), reduce the daily dosage by increasing the dosing interval and adjust as needed based upon therapeutic response and tolerability. Monitor renal function [see Dosage and Administration (2.2)] .

8.7 Hepatic Impairment

Avoid trimethobenzamide hydrochloride capsules in patients whose signs and symptoms suggest the presence of hepatic impairment due to the risk of hepatotoxicity [see Warnings and Precautions (5.4)] . Discontinue trimethobenzamide hydrochloride capsules in patients who develop impaired liver function while taking trimethobenzamide hydrochloride capsules.

11 DESCRIPTION

Chemically, trimethobenzamide hydrochloride is N-[ p-[2-(dimethylamino)ethoxy]benzyl]-3,4,5-trimethoxybenzamide monohydrochloride. It has a molecular weight of 424.93 and the following structural formula:

Capsules: Each capsule for oral use contains trimethobenzamide hydrochloride USP equivalent to 300 mg. The capsule has an opaque purple cap marked “HP” and an opaque purple body marked “180”. The inactive ingredients are lactose monohydrate, magnesium stearate, and corn starch. The capsule shell contains the following ingredients: gelatin, titanium dioxide, D&C Red No. 28, and FD&C Blue No. 1, and sodium lauryl sulfate.

White ink contains the following ingredients: Shellac, dehydrated alcohol, isopropyl alcohol, butyl alcohol, propylene glycol, ammonium hydroxide, potassium hydroxide and titanium dioxide.

12 CLINICAL PHARMACOLOGY

12.1 Mechanism of Action

The mechanism of action of trimethobenzamide as determined in animals is obscure, but may involve the chemoreceptor trigger zone (CTZ), an area in the medulla oblongata through which emetic impulses are conveyed to the vomiting center; direct impulses to the vomiting center apparently are not similarly inhibited. In dogs pretreated with trimethobenzamide HCl, the emetic response to apomorphine is inhibited, while little or no protection is afforded against emesis induced by intragastric copper sulfate.

12.3 Pharmacokinetics

Absorption

The pharmacokinetics of trimethobenzamide in healthy adult subjects were compared when trimethobenzamide hydrochloride capsule was administered as a 300 mg oral capsule or a 200 mg (100 mg/mL) intramuscular injection. The time to reach maximum plasma concentration (Tmax) was about 30 minutes after intramuscular injection compared to about 45 minutes after oral capsule administration. The plasma concentration-time profile of trimethobenzamide was similar between the two formulations.

Elimination

The mean elimination half-life of trimethobenzamide is 7 to 9 hours.

Metabolism

The major pathway of trimethobenzamide metabolism is through oxidation resulting in the formation of trimethobenzamide N-oxide metabolite. The pharmacologic activity of this major metabolite has not been evaluated.

Excretion

Between 30 to 50% of a single dose in humans is excreted unchanged in the urine within 48 to 72 hours.

Specific Populations

Sex

Systemic exposure to trimethobenzamide was similar between men (N=40) and women (N=28). Following a single 300 mg capsule oral administration, the respective mean (SD) Cmaxof trimethobenzamide were 3.5 (1.1) and 4.2 (1.6) micrograms/mL in male and female subjects. The respective mean (SD) of AUC0-∞of trimethobenzamide were 10 (2.7) and 10.4 (2.7) micrograms×hour/mL in male and female subjects.

Race

Pharmacokinetics appeared to be similar for Caucasians (N=53) and African Americans (N=12). Following a single 300 mg capsule oral administration, the respective mean (SD) Cmaxof trimethobenzamide was 3.8 (1.3) micrograms/mL in Caucasians and 3.9 (1.7) micrograms/mL in African Americans. The respective mean (SD) AUC0-∞of trimethobenzamide was 10.4 (2.8) micrograms×hour/mL in Caucasians and 9.8 (2.5) micrograms×hour/mL in African Americans.

16 HOW SUPPLIED/STORAGE AND HANDLING

Trimethobenzamide Hydrochloride Capsules, USP are available as a capsule for oral use with an size ‘1’, two-piece purple opaque cap and purple opaque body, hard gelatin capsules, printed in white with “HP” on cap and in white with “180” on body, filled with white to off-white granular powder. Each capsule contains 300 mg of trimethobenzamide hydrochloride.

NDC Number Strength Package
62135-773-30 300 mg capsules bottles of 30
62135-773-90 300 mg capsules bottles of 90

Store at 20° to 25°C (68° to 77°F); excursions permitted between 15° to 30°C (59° to 86°F) [See USP Controlled Room Temperature].

17 PATIENT COUNSELING INFORMATION

Inform patients that trimethobenzamide hydrochloride capsules can cause serious adverse reactions. Instruct patients to discontinue trimethobenzamide hydrochloride capsules and contact a healthcare provider immediately if the following serious reactions occur:

- Acute Dystonic Reactions and Other Extrapyramidal Symptoms [see Warnings and Precautions (5.1)]
- Other CNS Reactions [see Warnings and Precautions (5.2, 5.3)]
- Hepatotoxicity [see Warnings and Precautions (5.4)]

Effects on the Ability to Drive or Operate Machinery

Advise patients that trimethobenzamide hydrochloride capsules can cause drowsiness and may impair their judgment, thinking, or motor skills required for tasks such as driving a motor vehicle or operating machinery. Inform patients not to operate motor vehicles or other dangerous machinery until they are reasonably certain that trimethobenzamide hydrochloride capsules do not affect them adversely [see Warnings and Precautions (5.5)] .

Drug Interactions

Inform patients that use of alcohol or concomitant treatment with other CNS-acting drugs can precipitate or worsen CNS depression and/or EPS [see Drug Interactions (7.1, 7.2)] . Instruct patients avoid alcohol and to tell their health care providers when they start taking any concomitant medication.

Manufactured for:
Chartwell RX, LLC.
Congers, NY 10920

L71695

Revised 10/2023

PACKAGE LABEL.PRINCIPAL DISPLAY PANEL

Trimethobenzamide Hydrochloride Capsules, USP 300 mg - NDC - 62135-773-30 - 30's - Bottle Label

Trimethobenzamide Hydrochloride Capsules, USP 300 mg - NDC - 62135-773-90 - 90's - Bottle Label